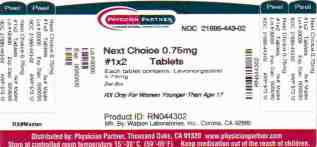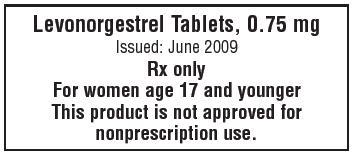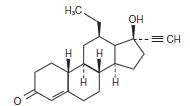 DRUG LABEL: NEXT CHOICE
                        
NDC: 21695-443 | Form: TABLET
Manufacturer: Rebel Distributors Corp.
Category: prescription | Type: HUMAN PRESCRIPTION DRUG LABEL
Date: 20090701

ACTIVE INGREDIENTS: LEVONORGESTREL 0.75 mg/1 1
INACTIVE INGREDIENTS: COLLOIDAL SILICON DIOXIDE; STARCH, CORN; FD&C YELLOW NO. 6; MAGNESIUM STEARATE; POVIDONE; LACTOSE MONOHYDRATE

Levonorgestrel Tablets, 0.75 mg

PHYSICIAN LABELING

Levonorgestrel Tablets, 0.75 mg

Rx only for women age 17 and younger

This product is not approved for nonprescription use.

Levonorgestrel tablets are a prescription–only emergency contraceptive for women age 17 and younger. This product is not approved for nonprescription use. Levonorgestrel tablets are intended to prevent pregnancy after known or suspected contraceptive failure or unprotected intercourse. Emergency contraceptive pills (like all oral contraceptives) do not protect against infection with HIV (the virus that causes AIDS) and other sexually transmitted diseases.

DESCRIPTION

Emergency contraceptive tablet. Each levonorgestrel tablet contains 0.75 mg of a single active steroid ingredient, levonorgestrel [18,19-Dinorpregn-4-en-20-yn-3-one-13-ethyl-17-hydroxy-, (17α)-(-)-], a totally synthetic progestogen. The inactive ingredients present are colloidal silicon dioxide, corn starch, FD&C Yellow #6, magnesium stearate, povidone, and lactose monohydrate. Levonorgestrel has a molecular weight of 312.45, and the following structural and molecular formulas:

C21H28O2

CLINICAL PHARMACOLOGY

Emergency contraceptives are not effective if the woman is already pregnant. Levonorgestrel tablets are believed to act as an emergency contraceptive principally by preventing ovulation or fertilization (by altering tubal transport of sperm and/or ova). In addition, they may inhibit implantation (by altering the endometrium). They are not effective once the process of implantation has begun.

Pharmacokinetics

Absorption

No specific investigation of the absolute bioavailability of levonorgestrel tablets in humans has been conducted. However, literature indicates that levonorgestrel is rapidly and completely absorbed after oral administration (bioavailability about 100%) and is not subject to first pass metabolism. After a single dose of levonorgestrel tablets (0.75 mg) administered to 16 women under fasting conditions, maximum serum concentrations of levonorgestrel are 14.1 ± 7.7 ng/mL (mean ± SD) at an average of 1.6 ± 0.7 hours. No formal study of the effect of food on the absorption of levonorgestrel has been undertaken.

Table 1 Pharmacokinetic Parameter Values Following Single Dose Administration of Levonorgestrel Tablets, 0.75 mg to Healthy Female Volunteers
 | Mean (± S.D.)
N | Cmax (ng/mL) | Tmax (h) | CL (L/h) | Vd (L) | T1/2 (h) | AUC0-∞ (ng/mL/h)
16 | 14.1 ± 7.7 | 1.6 ± 0.7 | 7.7 ± 2.7 | 260.0 | 24.4 ± 5.3 | 123.1 ± 50.1

Distribution

Levonorgestrel in serum is primarily protein bound. Approximately 50% is bound to albumin and 47.5% is bound to sex hormone binding globulin (SHBG).

Metabolism

Following a single oral dosage, levonorgestrel does not appear to be extensively metabolized by the liver. The primary metabolites are 3α,5β- and 3α,5α-tetrahydrolevonorgestrel with 16β-hydroxynorgestrel also identified. Together, these account for less than 10% of parent plasma levels. Urinary metabolites hydroxylated at the 2α and 16β positions have also been identified. Small amounts of the metabolites are present in plasma as sulfate and glucuronide conjugates.

Excretion

The elimination half-life of levonorgestrel following single dose administration as levonorgestrel tablets (0.75 mg) is 24.4 ± 5.3 hours. Excretion following single dose administration as emergency contraception is unknown, but based on chronic, low-dose contraceptive use, levonorgestrel and its metabolites are primarily excreted in the urine, with smaller amounts recovered in the feces.

SPECIAL POPULATIONS

Geriatric

This product is not intended for use in geriatric (age 65 years or older) populations and pharmacokinetic data are not available for this population.

Pediatric

This product is not intended for use in pediatric (premenarcheal) populations, and pharmacokinetic data are not available for this population.

Race

No formal studies have evaluated the effect of race. However, clinical trials demonstrated a higher pregnancy rate in the Chinese population with both levonorgestrel tablets and the Yuzpe regimen (another form of emergency contraception consisting of two doses of ethinyl estradiol 0.1 mg + levonorgestrel 0.5 mg). The reason for this apparent increase in the pregnancy rate of emergency contraceptives in Chinese women is unknown.

Hepatic Insufficiency and Renal Insufficiency

No formal studies have evaluated the effect of hepatic insufficiency or renal insufficiency on the disposition of emergency contraceptive tablets.

Drug-Drug Interactions

No formal studies of drug-drug interactions were conducted.

INDICATIONS AND USAGE

Levonorgestrel tablets are a prescription-only emergency contraceptive, for women age 17 and younger, that can be used to prevent pregnancy following unprotected intercourse or a known or suspected contraceptive failure. This product is not approved for nonprescription use.

To obtain optimal efficacy, the first tablet should be taken as soon as possible within 72 hours of intercourse. The second tablet must be taken 12 hours later.

Clinical Studies

A double-blind, controlled clinical trial in 1,955 evaluable women compared the efficacy and safety of levonorgestrel tablets, (one 0.75 mg tablet of levonorgestrel taken within 72 hours of intercourse, and one tablet taken 12 hours later) to the Yuzpe regimen (two tablets of 0.25 mg levonorgestrel and 0.05 mg ethinyl estradiol, taken within 72 hours of intercourse, and two tablets taken 12 hours later). Levonorgestrel tablets, were at least as effective as the Yuzpe regimen in preventing pregnancy. After a single act of intercourse, the expected pregnancy rate of 8% (with no contraception) was reduced to approximately 1% with levonorgestrel tablets.

Emergency contraceptives are not as effective as routine contraception since their failure rate, while low based on a single use, would accumulate over time with repeated use (see WARNINGS). See Table 2 below.

Table 2 Percentage of women experiencing an unintended pregnancy during the first year of typical use and the first year of perfect use of contraception, and the percentage continuing use at the end of the first year, United States.
 | % of Women Experiencing an Unintended Pregnancy within the First Year of Use |  | % of Women Continuing Use at One Year^3
Method (1) | Tpical Use^1 (2) | Perfect Use^2 (3) | (4)
Chance^4 | 85 | 85
Spermicide^5 | 26 | 6 | 40
Periodic Abstinence | 25 |  | 63
Calendar |  | 9
Ovulation Method |  | 3
Sympto-thermal^6 |  | 2
Post-ovulation |  | 1
Withdrawal | 19 | 4
Cap^7
Parous Women | 40 | 26 | 42
Nulliparous Women | 20 | 9 | 56
Sponge
Parous Women | 40 | 20 | 42
Nulliparous Women | 20 | 9 | 56
Diaphragm^7 | 20 | 6 | 56
Condom^8
Female (Reality®*) | 21 | 5 | 56
Male | 14 | 3 | 61
Pill | 5 |  | 71
Progestin Only |  | 0.5
Combined 0.1 |  | 0.1
IUD
Progesterone T | 2.0 | 1.5 | 81
Copper T 380A | 0.8 | 0.6 | 78
LNg 20 | 0.1 | 0.1 | 81
Depo-Provera®* | 0.3 | 0.3 | 70
Norplant®* and Norplant-2®* | 0.05 | 0.05 | 88
Female Sterilization | 0.5 | 0.5 | 100
Male Sterilization | 0.15 | 0.10 | 100
Emergency Contraceptive Pills: Treatment initiated within 72 hours after unprotected intercourse reduces the risk of pregnancy by at least 75%.^9
Lactational Amenorrhea Method: LAM is a highly effective, temporary, method of contraception.^10
Source: Trussell J, Contraceptive efficacy. In Hatcher RA, Trussell J, Stewart F, Cates W, Stewart GK, Kowal D, Guest F, Contraceptive Technology: Seventeenth Revised Edition. New York, NY: Irvington Publishers, 1998.
^1 Among typical couples who initiate use of a method (not necessarily for the first time), the percentage who experience an unintended pregnancy during the first year if they do not stop use for any other reason.
^2 Among couples who initiate use of a method (not necessarily for the first time) and who use it perfectly (both consistently and correctly), the percentage who experience an unintended pregnancy during the first year if they do not stop use for any other reason.
^3 Among couples attempting to avoid pregnancy, the percentage who continue to use a method for one year.
^4 The percentages of women becoming pregnant in columns (2) and (3) are based on data from populations where contraception is not used and from women who cease using contraception in order to become pregnant. Among such populations, about 89% become pregnant within one year. This estimate was lowered slightly (to 85%) to represent the percentage who would become pregnant within one year among women now relying on reversible methods of contraception if they abandoned contraception altogether.
^5 Foams, creams, gels, vaginal suppositories and vaginal film.
^6 Cervical mucus (ovulation) method supplemented by calendar in the preovulatory and basal body temperature in the post-ovulatory phases.
^7 With spermicidal cream or jelly.
^8 Without spermicides.
^9 The treatment schedule is one dose within 72 hours after unprotected intercourse and a second dose 12 hours after the first dose. The Food and Drug Administration has declared the following brands of oral contraceptives to be safe and effective for emergency contraception: Ovral®* (1 dose is 2 white pills), Alesse®* (1 dose is 5 pink pills), Nordette®* or Levlen®* (1 dose is 2 light-orange pills), Lo/Ovral®* (1 dose is 4 white pills), Triphasil®* or Tri-Levlen®* (1 dose is 4 yellow pills).
^10 However, to maintain effective protection against pregnancy, another method of contraception must be used as soon as menstruation resumes, the frequency or duration of breastfeeds is reduced, bottle feeds are introduced or the baby reaches six months of age.

CONTRAINDICATIONS

Progestin-only contraceptive pills (POPs) are used as a routine method of birth control over longer periods of time, and are contraindicated in some conditions. It is not known whether these same conditions apply to the levonorgestrel tablets regimen consisting of the emergency use of two progestin pills. POPs however, are not recommended for use in the following conditions:

- Known or suspected pregnancy
- Hypersensitivity to any component of the product

WARNINGS

Levonorgestrel tablets are not recommended for routine use as a contraceptive.
Levonorgestrel tablets are not effective in terminating an existing pregnancy.

Effects on Menses

Menstrual bleeding patterns are often irregular among women using progestin-only oral contraceptives and in clinical studies of levonorgestrel for postcoital and emergency contraceptive use. Some women may experience spotting a few days after taking levonorgestrel tablets. At the time of expected menses, approximately 75% of women using levonorgestrel tablets had vaginal bleeding similar to their normal menses, 12% to 13% bled more than usual, and 12% bled less than usual. The majority of women (87%) had their next menstrual period at the expected time or within ± 7 days, while 13% had a delay of more than 7 days beyond the anticipated onset of menses. If there is a delay in the onset of menses beyond 1 week, the possibility of pregnancy should be considered.

Ectopic Pregnancy

Ectopic pregnancies account for approximately 2% of reported pregnancies (19.7 per 1,000 reported pregnancies). Up to 10% of pregnancies reported in clinical studies of routine use of progestin-only contraceptives are ectopic. A history of ectopic pregnancy need not be considered a contraindication to use of this emergency contraceptive method. Health providers, however, should be alert to the possibility of an ectopic pregnancy in women who become pregnant or complain of ower abdominal pain after taking levonorgestrel tablets.

PRECAUTIONS

Pregnancy

Many studies have found no effects on fetal development associated with long-term use of contraceptive doses of oral progestins (POPs). The few studies of infant growth and development that have been conducted with POPs have not demonstrated significant adverse effects.

STD/HIV

Levonorgestrel tablets, like progestin-only contraceptives, do not protect against HIV infection (AIDS) and other sexually transmitted diseases.

Physical Examination and Follow-up

A physical examination is not required prior to prescribing levonorgestrel tablets. A follow-up physical or pelvic examination, however, is recommended if there is any doubt concerning the general health or pregnancy status of any woman after taking levonorgestrel tablets.

Carbohydrate Metabolism

The effects of levonorgestrel tablets on carbohydrate metabolism are unknown. Some users of progestin-only oral contraceptives (POPs) may experience slight deterioration in glucose tolerance, with increases in plasma insulin; however, women with diabetes mellitus who use POPs do not generally experience changes in their insulin requirements. Nonetheless, diabetic women should be monitored while taking levonorgestrel tablets.

Drug Interactions

Theoretically, the effectiveness of low-dose progestin-only pills is reduced by hepatic enzyme-inducing drugs such as the anticonvulsants phenytoin, carbamazepine, and barbiturates, and the antituberculosis drug rifampin. No significant interaction has been found with broad-spectrum antibiotics. It is not known whether the efficacy of levonorgestrel tablets would be affected by these or any other medications.

Nursing Mothers

Small amounts of progestin pass into the breast milk in women taking progestinonly pills for long-term contraception resulting in steroid levels in infant plasma of 1% to 6% of the levels of maternal plasma. However, no adverse effects due to progestin-only pills have been found on breastfeeding performance, either in the quality or quantity of the milk, or on the health, growth or development of the infant.

Pediatric Use

Safety and efficacy of progestin-only pills have been established in women of reproductive age for long-term contraception. Safety and efficacy are expected to be the same for postpubertal adolescents under the age of 16 and for users 16 years and older. Use of levonorgestrel tablets emergency contraception before menarche is not indicated.

Fertility Following Discontinuation

The limited available data indicate a rapid return of normal ovulation and fertility following discontinuation of progestin-only pills for emergency contraception and long-term contraception.

ADVERSE REACTIONS

The most common adverse events in the clinical trial for women receiving levonorgestrel tablets included nausea (23%), abdominal pain (18%), fatigue (17%), headache (17%), and menstrual changes. The table below shows those adverse events that occurred in ≥5% of levonorgestrel tablets users.

Table 3 Adverse Events in ≥5% of Women, by % Frequency
Most Common Adverse Events | Levonorgestrel N=977 (%)
Nausea | 23.1
Abdominal Pain | 17.6
Fatigue | 16.9
Headache | 16.8
Heavier Menstrual Bleeding | 13.8
Lighter Menstrual Bleeding | 12.5
Dizziness | 11.2
Breast Tenderness | 10.7
Other complaints | 9.7
Vomiting | 5.6
Diarrhea | 5.0

Levonorgestrel tablets demonstrated a superior safety profile over the Yuzpe regimen for the following adverse events:

- Nausea: Occurred in 23% of women taking levonorgestrel tablets (compared to 50% with Yuzpe)
- Vomiting: Occurred in 6% of women taking levonorgestrel tablets (compared to 19% with Yuzpe)

DRUG ABUSE AND DEPENDENCE

There is no information about dependence associated with the use of levonorgestrel tablets.

OVERDOSAGE

There are no data on overdosage of levonorgestrel tablets, although the common adverse event of nausea and its associated vomiting may be anticipated.

DOSAGE AND ADMINISTRATION

One levonorgestrel tablet should be taken orally as soon as possible within 72 hours after unprotected intercourse. The second tablet should be taken 12 hours after the first dose. Efficacy is better if levonorgestrel tablets are taken as directed as soon as possible after unprotected intercourse. Levonorgestrel tablets can be used at any time during the menstrual cycle.

The user should be instructed that if she vomits within one hour of taking either dose of medication she should contact her health care professional to discuss whether to repeat that dose.

HOW SUPPLIED

Levonorgestrel Tablets, 0.75 mg are available for a single course of treatment in PVC/aluminum foil blister packages of two tablets each. Each tablet is peach, round, bevel edged, and flat faced embossed with “475” on one side and “WATSON” on the other side.

Available as:

Unit-of-use NDC 0591-0475-36

Store levonorgestrel tablets at controlled room temperature, 20° to 25°C (68° to 77°F); excursions permitted between 15° to 30°C (59° to 86°F) [See USP].

*The following are registered trademarks of their respective manufacturers: Reality® is manufactured by Female Health Company and a registered trademark of Meijer, Inc.; Depo-Provera® is manufactured by and a registered trademark of Pharmacia and Upjohn; Norplant® is manufactured by and a registered trademark of Population Council; Ovral®, Alesse®, Triphasil® and Lo Ovral®/Wyeth Pharmaceuticals, Inc.; Nordette®/Duramed Pharmaceuticals, Inc.; Levlen® and Tri- Levlen®/Bayer Healthcare.

Watson Laboratories, Inc.
Corona, CA 92880 USA
Phone: 1-800-272-5525
14816-3

Repackaged by:
Rebel Distributors Corp.
Thousand Oaks, CA 91320